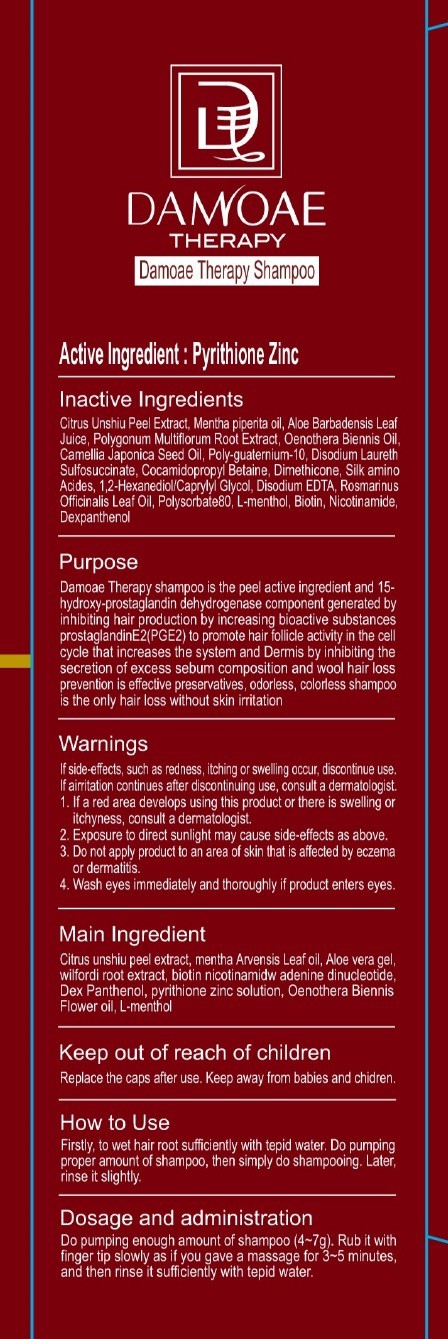 DRUG LABEL: DAMOAE THERAPY
NDC: 76081-010 | Form: SHAMPOO
Manufacturer: DUALLIFE CO., LTD.
Category: otc | Type: HUMAN OTC DRUG LABEL
Date: 20110720

ACTIVE INGREDIENTS: PYRITHIONE ZINC 3 g/300 g
INACTIVE INGREDIENTS: biotin; NIACINAMIDE; Dexpanthenol; DISODIUM LAURETH SULFOSUCCINATE; COCAMIDOPROPYL BETAINE; POLYSORBATE 80; MENTHA PIPERITA LEAF; CITRUS RETICULATA FRUIT OIL; ALOE VERA LEAF; FALLOPIA MULTIFLORA ROOT; POLYQUATERNIUM-10 (400 CPS AT 2%); DIMETHICONE; ROSEMARY OIL; OENOTHERA BIENNIS FLOWERING TOP; LEVOMENTHOL; 1,2-HEXANEDIOL; CAPRYLYL GLYCOL; WATER

Drug Facts

Active ingredient: PYRITHIONE ZINC

Inactive ingredients:

biotin, Dexpanthenol, DISODIUM LAURETH SULFOSUCCINATE, COCAMIDOPROPYL BETAINE, POLYSORBATE 80, MENTHA PIPERITA LEAF, CITRUS RETICULATA FRUIT OIL,
ALOE VERA LEAF, FALLOPIA MULTIFLORA ROOT, POLYQUATERNIUM-10 (400 CPS AT 2%), DIMETHICONE, ROSEMARY OIL, OENOTHERA BIENNIS FLOWERING TOP, LEVOMENTHOL,
1,2-HEXANEDIOL, CAPRYLYL GLYCOL, WATER

Purpose: Dandruff

Warnings:

If side-effects, such as redness, itching or swelling occur, discontinue use. If a irritation continues after discontinuing use, consult a dermatologist.
If a red area develops using this product or there is swelling or itchiness, consult a dermatologist.
Exposure to direct sunlight may cause side-effects as above.
Do not apply product to an area of skin that is affected by eczema or dermatitis.
Wash eyes immediately and thoroughly if product enters eyes.

Keep out of reach of children:

Replace the caps after use.
Keep away from babies and children.

Indication and usage:

Firstly, to wet hair root sufficiently with tepid water. Do pumping proper amount of shampoo, then simply do shampooing. Later, rinse it slightly.

Dosage and administration:

Do pumping enough amount of shampoo. Rub it with finger tip slowly as if you gave a massage for 3-5 minutes, and then rinse it sufficiently with tepid water.